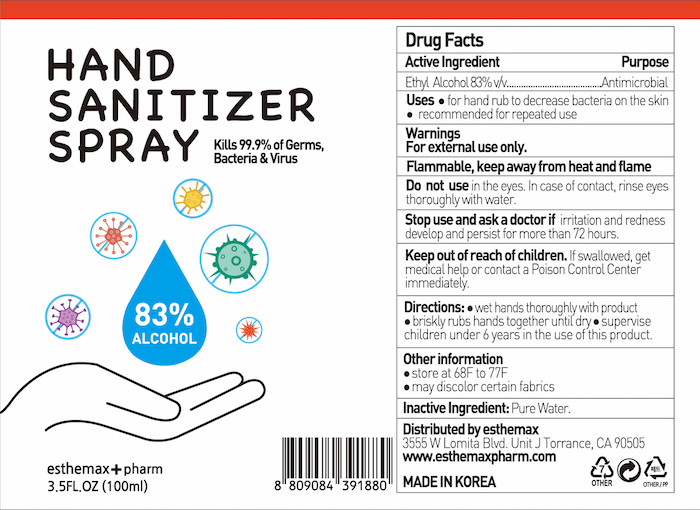 DRUG LABEL: esthemax pharm Hand Sanitizer
NDC: 74926-0010 | Form: GEL
Manufacturer: K Beauty Inc
Category: otc | Type: HUMAN OTC DRUG LABEL
Date: 20210312

ACTIVE INGREDIENTS: ALCOHOL 83 mL/100 mL
INACTIVE INGREDIENTS: GLYCERIN; WATER

esthemax pharm hand sanitizer

Active Ingredient

Ethyl Alcohol 83.0 %

Purpose

Antimicrobial

Warnings

Flammable. Keep away from fire or flame. For external use only.

When using this product do not use in or near the eyes.

In case of contact, rinse eyes thoroughly with water.

Stop use and ask a doctor if irritation or rash appears and lasts.

Keep out of reach of children. If swallowed, get medical help or contact a Poison Control Center right away.

Keep out of reach of children.

Directions

Place enough product in the palm of your hands to thoroughly cover your hands. Rub hands together briskly until product is completely absorbed and hands are dry.

DOSAGE AND ADMINISTRATION

Place enough product in the palm of your hands to thoroughly cover you hands. Rub hands together briskly until product is completely absorbed and hands are dry.

Inactive Ingredients:

Inactive Ingredients

Inactive Ingredient: water